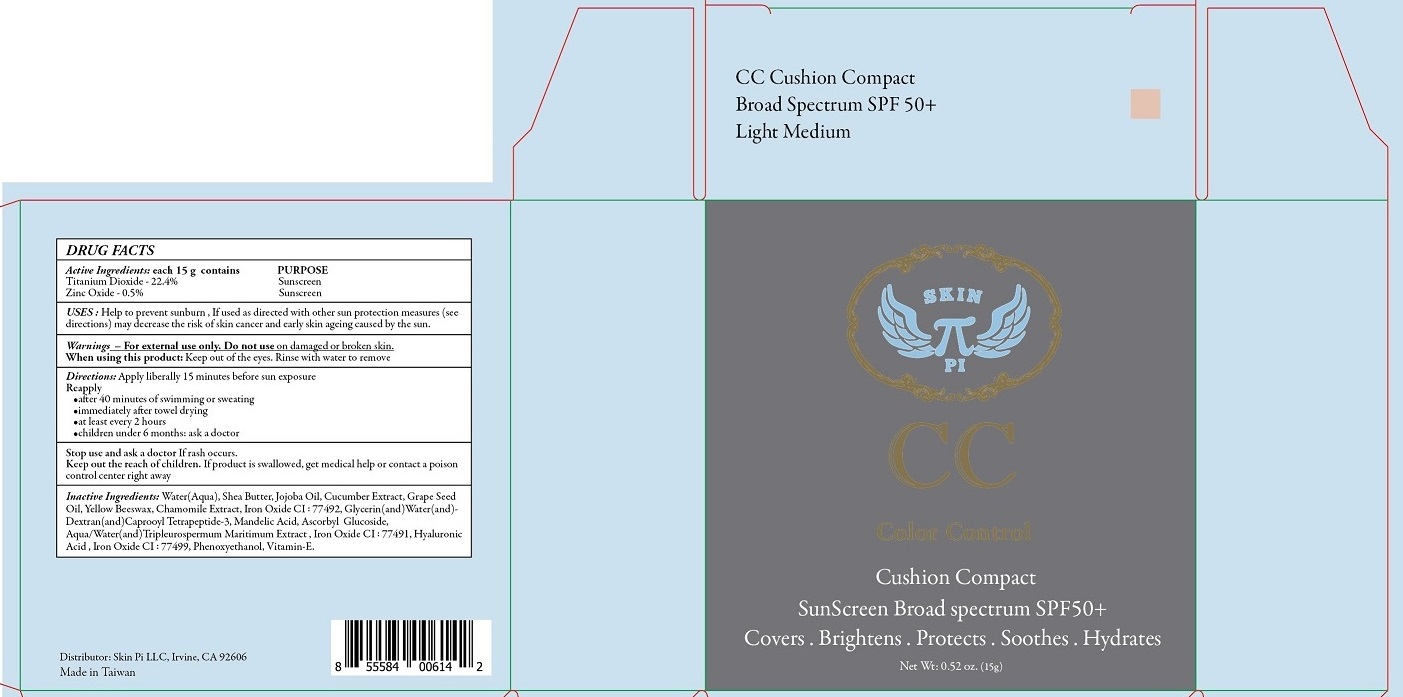 DRUG LABEL: CC Cushion Compact SunScreen - light / medium
NDC: 71190-6487 | Form: CREAM
Manufacturer: Skin Pi LLC
Category: otc | Type: HUMAN OTC DRUG LABEL
Date: 20170120

ACTIVE INGREDIENTS: TITANIUM DIOXIDE 22.4 g/100 g; ZINC OXIDE 0.5 g/100 g
INACTIVE INGREDIENTS: WATER; SHEA BUTTER; JOJOBA OIL; CUCUMBER; GRAPE SEED OIL; YELLOW WAX; CHAMOMILE; FERRIC OXIDE YELLOW; GLYCERIN; DEXTRAN 40; CAPROOYL TETRAPEPTIDE-3; MANDELIC ACID; ASCORBYL GLUCOSIDE; TRIPLEUROSPERMUM INODORUM WHOLE; FERRIC OXIDE RED; HYALURONIC ACID; FERROSOFERRIC OXIDE; PHENOXYETHANOL; .ALPHA.-TOCOPHEROL

CC Cushion Compact SunScreen - Light / Medium

Active Ingredients: each 15 g contains

Titanium Dioxide - 22.4%

Zinc Oxide - 0.5%

PURPOSE

Sunscreen

INDICATIONS AND USAGE

USES: Help to prevent sunburn. If used as directed with other sun protection measures (see directions) may decrease the risk of skin cancer and early skin ageing caused by the sun.

WARNINGS

Warnings - For external use only. Do not use on damaged or broken skin.
When using this product: Keep out of the eyes. Rinse with water to remove
Stop use and ask a doctor If rash occurs.

KEEP OUT OF REACH OF CHILDREN

Keep out the reach of children. If product is swallowed, get medical help or contact a poison control center right away.

DOSAGE AND ADMINISTRATION

Directions: Apply liberally 15 minutes before sun exposure.

Reapply

- after 40 minutes of swimming or sweating
- immediately after towel drying
- atleast every 2 hours
- children under 6 months: ask a doctor.

INACTIVE INGREDIENT

Inactive Ingredients: Water(Aqua), Shea Butter, Jojoba Oil, Cucumber Extract, Grape Seed Oil, Yellow Beeswax, Chamomile Extract, Iron Oxide CI : 77492, Glycerin(and)Water (and) Dextran (and) Caprooyl Tetrapeptide-3, Mandelic Acid, Ascorbyl Glucoside, Aqua /Water (and) Tripleurospermum Maritimum Extract, Iron Oxide CI : 77491, Hyaluronic Acid, Iron Oxide CI : 77499, Phenoxyethanol, Vitamin-E.

Color Control

SunScreen Broad spectrum SPF50+

Covers . Brightens . Protects . Soothes . Hydrates